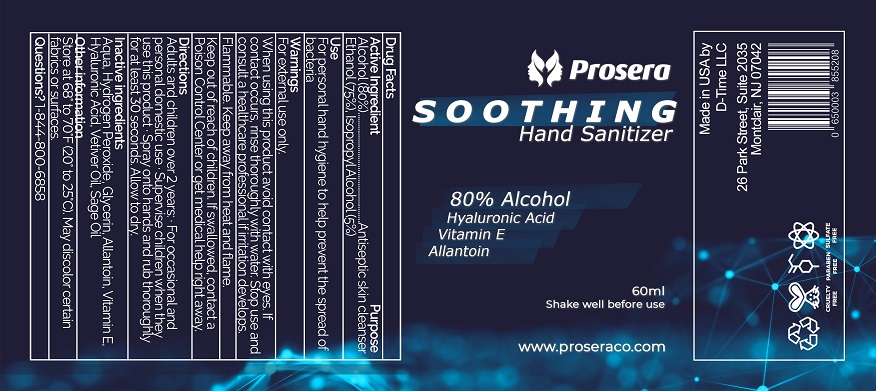 DRUG LABEL: Prosera Soothing Hand Sanitizer
NDC: 75306-002 | Form: LIQUID
Manufacturer: D-Time Limited Liability Company
Category: otc | Type: HUMAN OTC DRUG LABEL
Date: 20211102

ACTIVE INGREDIENTS: ALCOHOL 75 mL/100 mL; ISOPROPYL ALCOHOL 5 mL/100 mL
INACTIVE INGREDIENTS: HYDROGEN PEROXIDE; GLYCERIN; ALLANTOIN; .ALPHA.-TOCOPHEROL; HYALURONIC ACID; VETIVER OIL; SAGE OIL

Active Ingredient

Alcohol (80%)

Ethyl Alcohol (75%), Isopropyl Alcohol (5%)

Purpose

Antiseptic skin cleanser

Use

For personal hand hygiene to help prevent the spread of bacteria.

Warnings

For external use only.

When using this product avoid contact with eyes. If contact occurs, rinse thoroughly with water. Stop use and consult a healthcare professional if irritation develops.

Flammable. Keep away from heat and flame.

Keep out of reach of children. If swallowed, contact a Poison Control Center or , get medical help right away.

Directions

Adults and children over 2 years: ∙ For occasional and personal domestic use. Supervise children when they use this product. Spray onto hands and rub thoroughly for at least 30 seconds. Allow to dry.

Inactive ingredients

Aqua, Hydrogen Peroxide, Glycerin, Allantoin, Vitamin E, Hyaluronic Acid, Vetiver Oil, Sage Oil

Other information

Store at 68^0 to 70^0 F (20^0 to 25^0C). May discolor certain fabrics or surfaces.

Questions? 1-844-800-6858